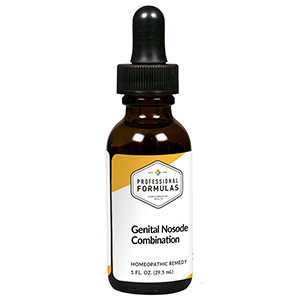 DRUG LABEL: Genital Nosode Combination
NDC: 63083-9406 | Form: LIQUID
Manufacturer: Professional Complementary Health Formulas
Category: homeopathic | Type: HUMAN OTC DRUG LABEL
Date: 20190815

ACTIVE INGREDIENTS: POTASSIUM SULFATE 4 [hp_X]/29.5 mL; VIOLA TRICOLOR WHOLE 4 [hp_X]/29.5 mL; GOLDENSEAL 5 [hp_X]/29.5 mL; WOOD CREOSOTE 6 [hp_X]/29.5 mL; DAPHNE MEZEREUM BARK 6 [hp_X]/29.5 mL; SODIUM CARBONATE 6 [hp_X]/29.5 mL; NITRIC ACID 6 [hp_X]/29.5 mL; SALMONELLA ENTERICA ENTERICA SEROVAR ENTERITIDIS 12 [hp_X]/29.5 mL; TRICHOMONAS VAGINALIS 12 [hp_X]/29.5 mL; 1,3-BIS(BENZOTHIAZOL-2-YLTHIOMETHYL)UREA 12 [hp_X]/29.5 mL
INACTIVE INGREDIENTS: ALCOHOL; WATER

R406

ACTIVE INGREDIENTS

Kali sulphuricum 4X
Viola tricolor 4X
Hydrastis canadensis 5X
Kreosotum 6X
Mezereum 6X
Natrum carbonicum 6X
Nitricum acidum 6X
Bacillus gaertner 12X
Trichomonas vaginalis 12X
Ureaplasma 12X

QUESTIONS

Professional Formulas

PO Box 2034 Lake Oswego, OR 97035

INDICATIONS

For the temporary relief of mild abdominal pain or discomfort, mental fatigue, occasional headache, anxiousness, or irritability.*

PURPOSE

*Claims based on traditional homeopathic practice, not accepted medical evidence. Not FDA evaluated.

WARNINGS

Persistent symptoms may be a sign of a serious condition. If symptoms persist or are accompanied by a fever, rash, or persistent headache, consult a doctor. Keep out of the reach of children. In case of overdose, get medical help or contact a poison control center right away. If pregnant or breastfeeding, ask a healthcare professional before use.

Keep out of the reach of children.

PREGNANCY OR BREAST FEEDING

If pregnant or breastfeeding, ask a healthcare professional before use.

DIRECTIONS

Place drops under tongue 30 minutes before/after meals. Adults and children 12 years and over: Take 10 to 15 drops once weekly or monthly. If mild symptoms are present, take 10 drops up to 3 times per day. Consult a physician for use in children under 12 years of age.

OTHER INFORMATION

Tamper resistant. If seal is broken, do not use. After opening, close container tightly and store at room temperature away from heat.

INACTIVE INGREDIENTS

40% ethanol, purified water.

LABEL

Est 1985

Professional Formulas

Complementary Health

Genital Nosode Combination

Homeopathic Remedy

1 FL. OZ. (29.5 mL)